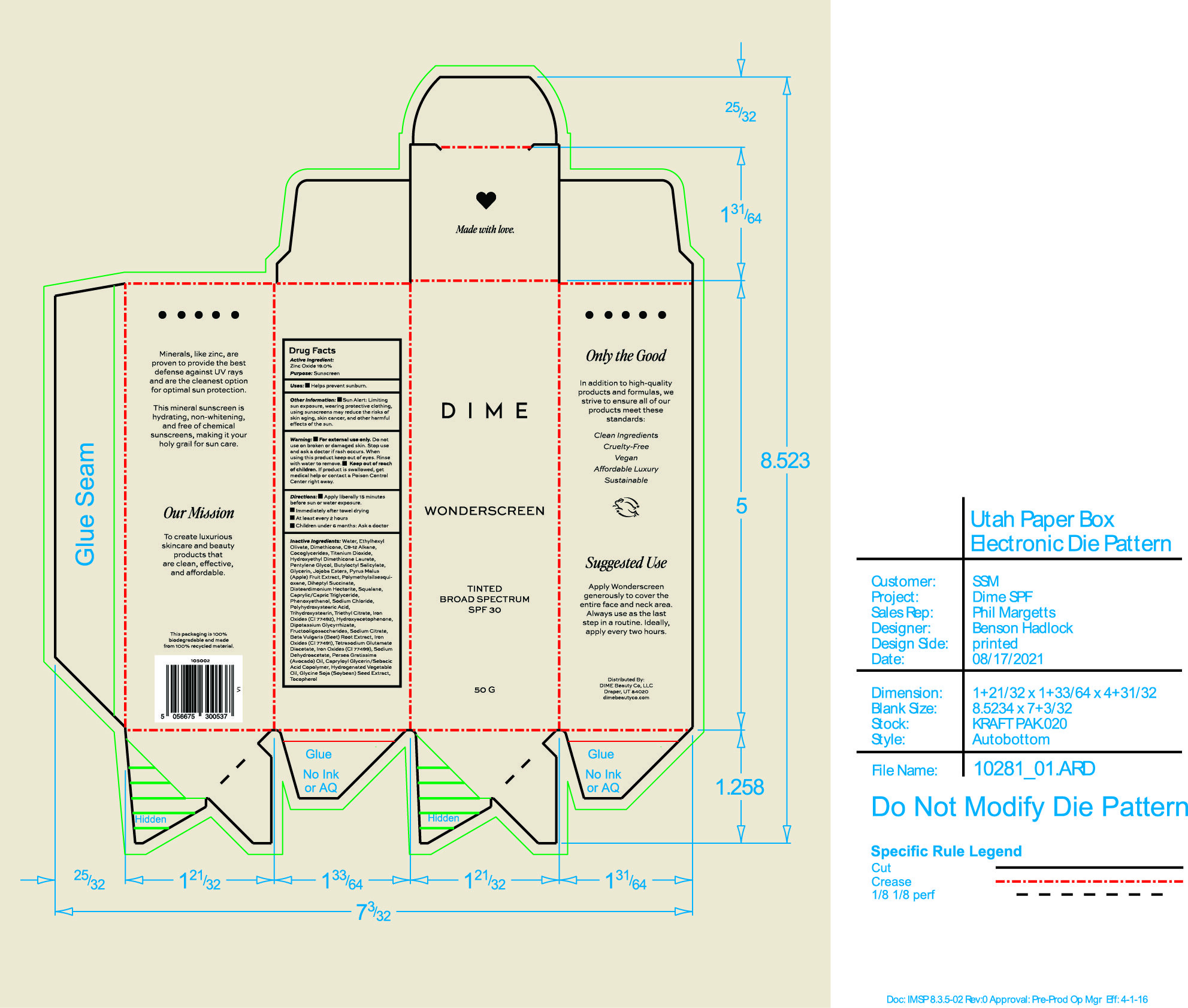 DRUG LABEL: Wonderscreen Broad Spectrum SPF 30 Shade 1
NDC: 82870-007 | Form: CREAM
Manufacturer: Dime Beauty Co, LLC
Category: otc | Type: HUMAN OTC DRUG LABEL
Date: 20251001

ACTIVE INGREDIENTS: ZINC OXIDE 19 g/100 g
INACTIVE INGREDIENTS: C9-12 ALKANE; HYDROXYACETOPHENONE; SODIUM DEHYDROACETATE; ETHYLHEXYL OLIVATE; JOJOBA OIL, RANDOMIZED; APPLE; FERRIC OXIDE YELLOW; AVOCADO OIL; GLYCYRRHIZINATE DIPOTASSIUM; TITANIUM DIOXIDE; POLYMETHYLSILSESQUIOXANE (4.5 MICRONS); DISTEARDIMONIUM HECTORITE; TETRASODIUM GLUTAMATE DIACETATE; CAPRYLOYL GLYCERIN/SEBACIC ACID COPOLYMER (2000 MPA.S); TOCOPHEROL; FERROSOFERRIC OXIDE; MEDIUM-CHAIN TRIGLYCERIDES; TRIETHYL CITRATE; FERRIC OXIDE RED; DIHEPTYL SUCCINATE; PHENOXYETHANOL; PENTYLENE GLYCOL; WATER; DIMETHICONE; COCO-GLYCERIDES; TRIHYDROXYSTEARIN; POLYHYDROXYSTEARIC ACID (2300 MW); BEET; BUTYLOCTYL SALICYLATE; GLYCERIN; SQUALANE; SODIUM CITRATE; SODIUM CHLORIDE

Wonderscreen Broad Spectrum SPF 30 Shade 1

Active ingredient: Zinc Oxide 19.0%

Purpose : Sunscreen

Uses

- Helps prevent sunburn

- Keep out of reach of children. If product is swallowed, get medical help or contact a Poison Control Center right away.

Stop use and ask a doctor if rash occurs.

Warning:

For External Use only. Do not use on broken or damaged skin. When using this product keep out of eyes. Rinse with water to remove

Directions:

- Apply liberally 15 minutes before sun or water exposure
- Immediately after towel drying
- At least every 2 hours
- Children under 6 months: Ask a doctor

INACTIVE INGREDIENT

Inactive Ingredients: Water, Ethylhexyl Olivate, Dimethicone, C9-12 Alkane, Cocoglycerides, Titanium Dioxide, Hydroxyethyl Dimethicone Laurate, Pentylene Glycol, Butyloctyl Salicylate, Glycerin, Jojoba Esters, Pyrus Malus (Apple) Fruit Extract, Polymethylsilsesquioxane, Diheptyl Succinate, Disteardimonium Hectorite, Squalane, Caprylic/Capric Triglyceride, Phenoxyethanol, Sodium Chloride, Polyhydroxystearic Acid, Trihydroxystearin, Triethyl Citrate, Iron Oxide (CI 77492), Hydroxyacetophenone, Dipotassium Glycyrrhizate, Fructooligosaccharides, Sodium Citrate, Beta Vulgaris (Beet) Root Extract, Iron Oxides (CI 77491), Tetrasodium Glutamate Diacetate, Iron Oxides (CI 77499), Sodium Dehydroacetate, Persea Gratissima (Avocado) Oil, Capryloyl Glycerin/Sebacic Acid Copolymer, Hydrogenated Vegetable Oil, Glycine Soja (Soybean) Seed Extract, Tocopherol

PACKAGE LABEL

Wonderscreen Tinted Broad Spectrum SPF 30

50 G